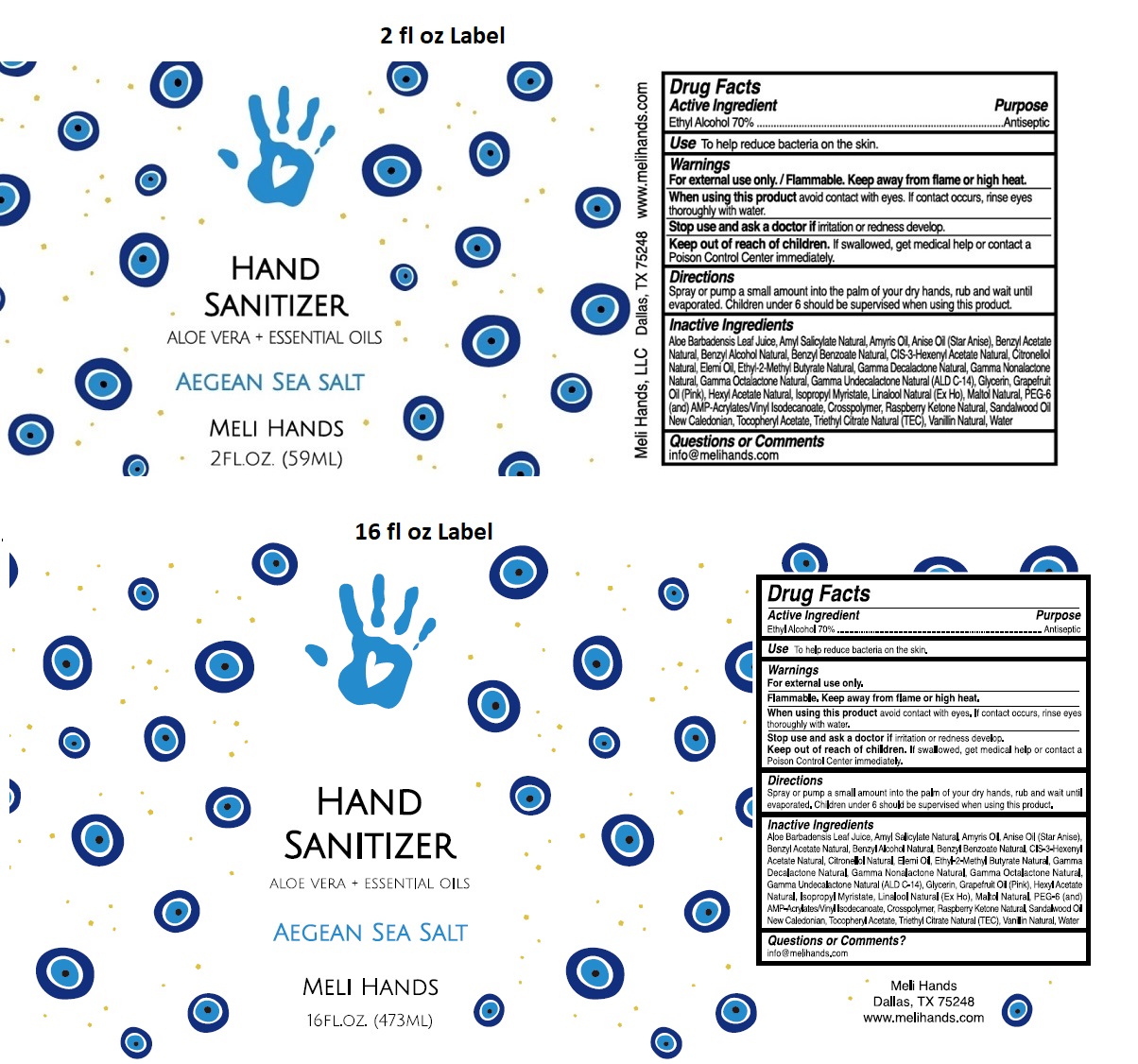 DRUG LABEL: MELI HANDS HAND SANITIZER
NDC: 79426-106 | Form: SPRAY
Manufacturer: MELI HANDS, LLC
Category: otc | Type: HUMAN OTC DRUG LABEL
Date: 20210922

ACTIVE INGREDIENTS: ALCOHOL 70 mL/100 mL
INACTIVE INGREDIENTS: ALOE VERA LEAF; AMYL SALICYLATE; AMYRIS BALSAMIFERA OIL; STAR ANISE OIL; BENZYL ACETATE; BENZYL ALCOHOL; BENZYL BENZOATE; 3-HEXENYL ACETATE, (3Z)-; .BETA.-CITRONELLOL, (R)-; ELEMI OIL; ETHYL 2-METHYLBUTYRATE; .GAMMA.-DECALACTONE; .GAMMA.-NONALACTONE; .GAMMA.-OCTALACTONE; .GAMMA.-UNDECALACTONE; GLYCERIN; GRAPEFRUIT OIL; HEXYL ACETATE; ISOPROPYL MYRISTATE; LINALOOL, (+/-)-; MALTOL; POLYETHYLENE GLYCOL 300; ACRYLATES/VINYL ISODECANOATE CROSSPOLYMER (10000 MPA.S NEUTRALIZED AT 0.5%); 4-(P-HYDROXYPHENYL)-2-BUTANONE; SANDALWOOD OIL; .ALPHA.-TOCOPHEROL ACETATE; TRIETHYL CITRATE; VANILLIN; WATER

MELI HANDS HAND SANITIZER AEGEAN SEA SALT

Active Ingredient

Ethyl Alcohol 70%

Purpose

Antiseptic

Use

To help reduce bacteria on the skin.

Warnings

For external use only./Flammable. Keep away from flame or high heat.

When using this product avoid contact with eyes. If contact occurs, rinse eyes thoroughly with water.

Stop use and ask doctor if irritation or redness develop.

Keep out of reach of children. If swallowed, get medical help or contact a Poison Control Center immediately.

Directions

Spray or pump a small amount into the palm of your dry hands, rub and wait until evaporated. Children under 6 should be supervised when using this product.

Inactive Ingredients

Aloe Barbadensis Leaf Juice, Amyl Salicylate Natural, Amyris Oil, Anise Oil (Star Anise), Benzyl Acetate Natural, Benzyl Alcohol Natural, Benzyl Benzoate Natural, CIS-3-Hexenyl Acetate Natural, Citronellol Natural, Elemi Oil, Ethyl-2-Methyl Butyrate Natural, Gamma Decalactone Natural, Gamma Nonalactone Natural, Gamma Octalactone Natural, Gamma Undecalactone Natural (ALD C-14), Glycerin, Grapefruit Oil (Pink), Hexyl Acetate Natural, Isopropyl Myristate, Linalool Natural (Ex Ho), Maltol Natural, PEG-6 (and) AMP-Acrylates/Vinyl Isodecanoate Crosspolymer, Raspberry Ketone Natural, Sandalwood Oil New Caledonian, Tocopheryl Acetate, Triethyl Citrate Natural (TEC), Vanillin Natural, Water

Questions or Comments

info@melihands.com

ALOE VERA + ESSENTIAL OILS

AEGEAN SEA SALT

Meli Hands, LLC Dallas, TX 75248 www.melihands.com